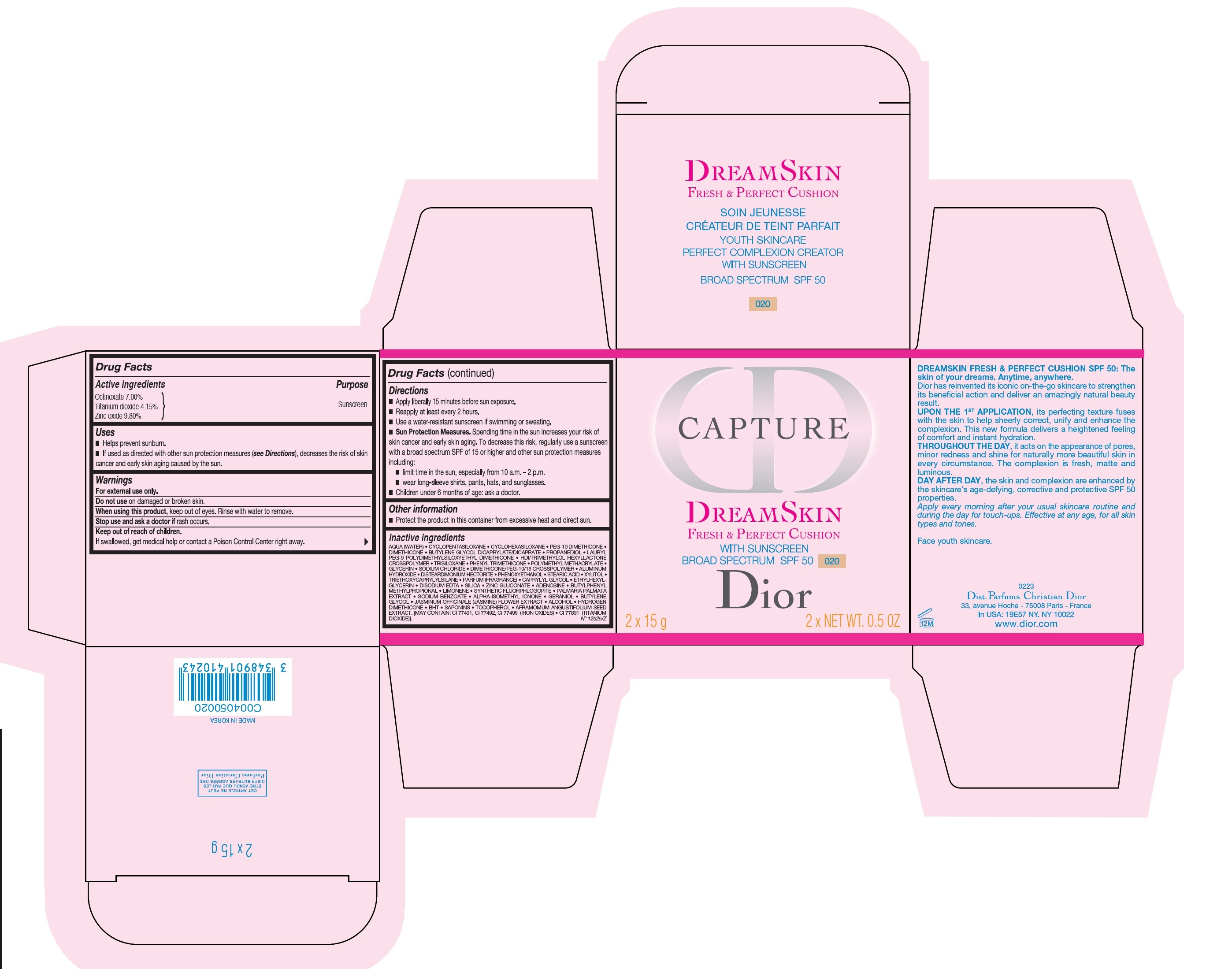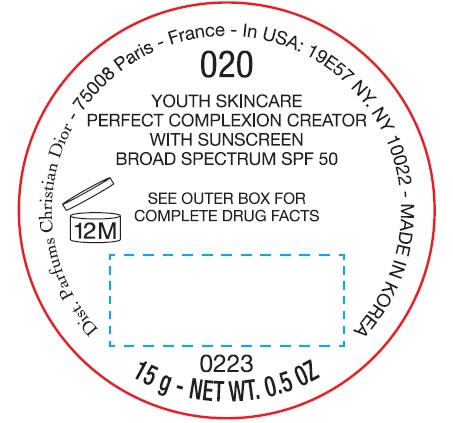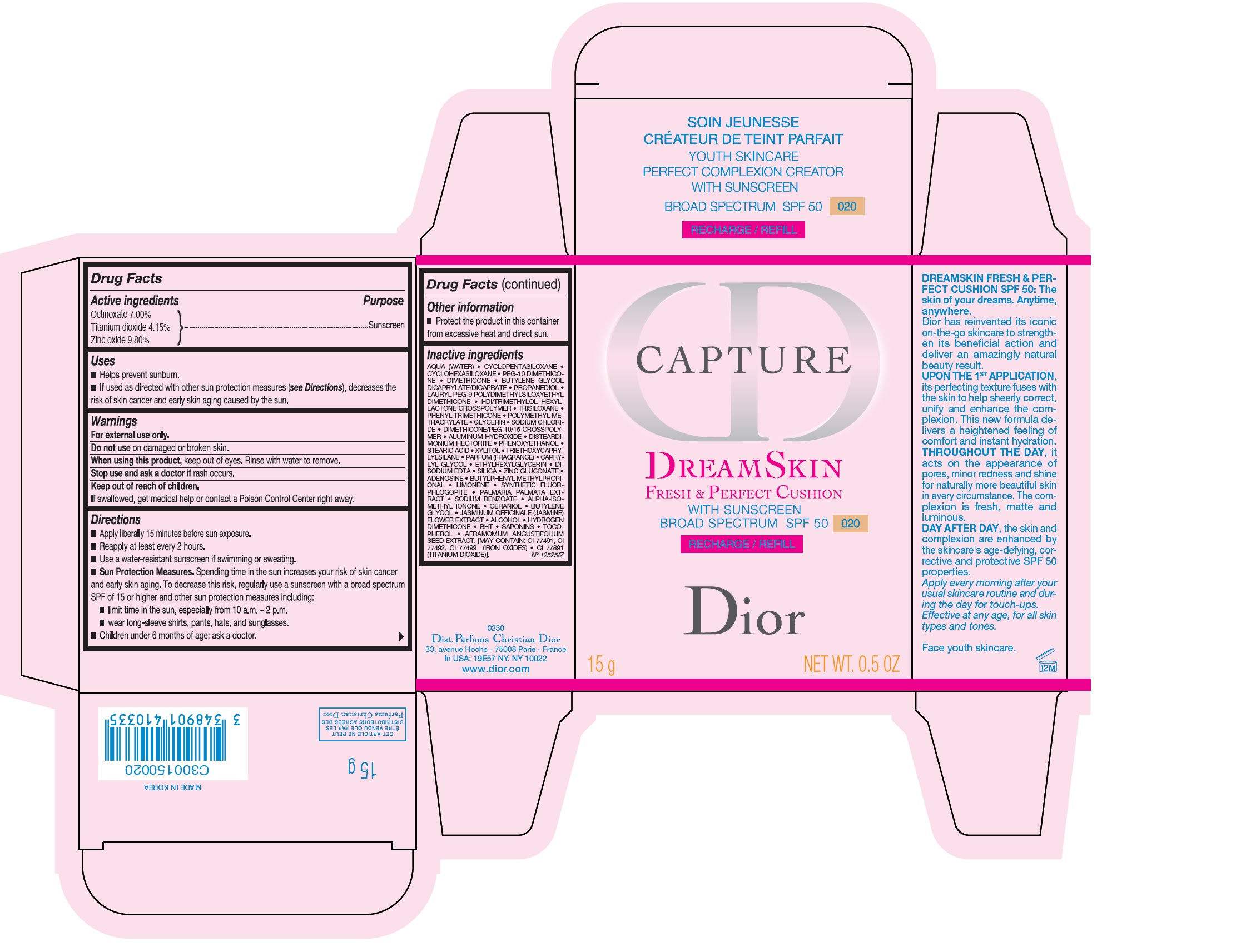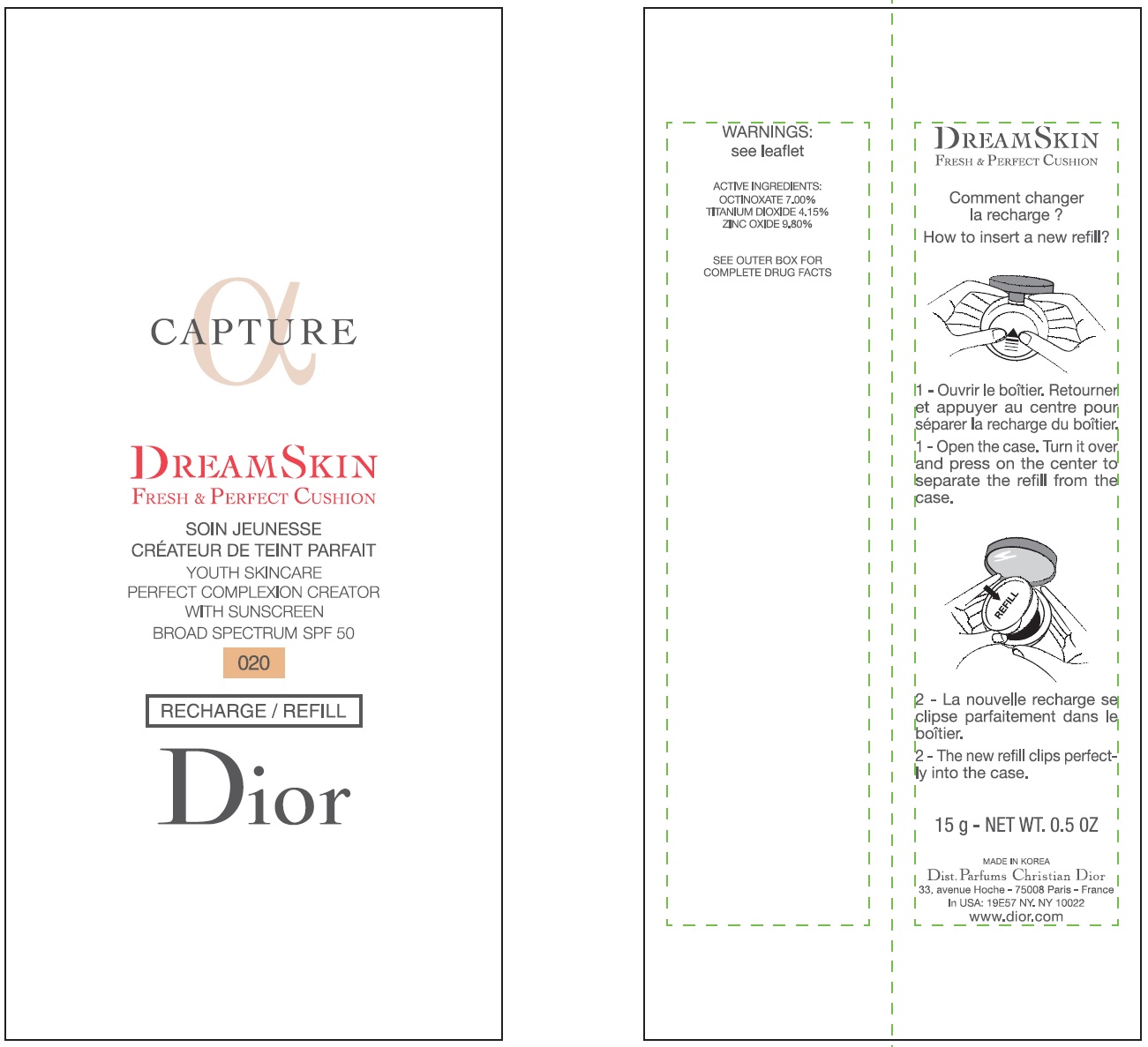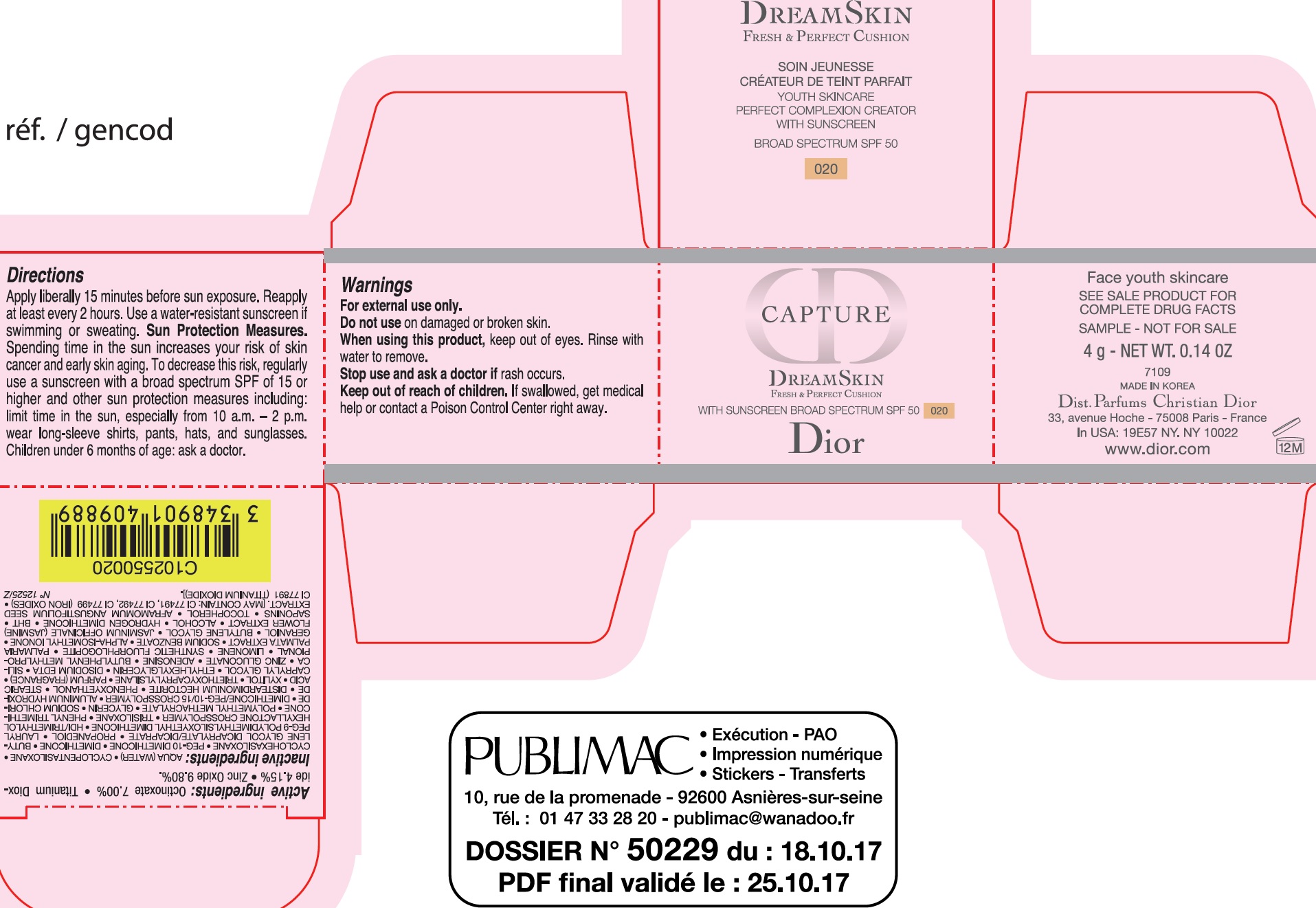 DRUG LABEL: CAPTURE DREAMSKIN FRESH AND PERFECT CUSHION WITH SUNSCREEN BROAD SPECTRUM SPF 50 020
NDC: 61957-2902 | Form: EMULSION
Manufacturer: Parfums Christian Dior
Category: otc | Type: HUMAN OTC DRUG LABEL
Date: 20250116

ACTIVE INGREDIENTS: OCTINOXATE 70 mg/1 g; TITANIUM DIOXIDE 41.5 mg/1 g; ZINC OXIDE 98 mg/1 g
INACTIVE INGREDIENTS: PHENYL TRIMETHICONE; GLYCERIN; SODIUM CHLORIDE; DISTEARDIMONIUM HECTORITE; ALUMINUM HYDROXIDE; PHENOXYETHANOL; STEARIC ACID; XYLITOL; TRIETHOXYCAPRYLYLSILANE; CAPRYLYL GLYCOL; ETHYLHEXYLGLYCERIN; EDETATE DISODIUM ANHYDROUS; SILICON DIOXIDE; ZINC GLUCONATE; ADENOSINE; BUTYLPHENYL METHYLPROPIONAL; LIMONENE, (+)-; DULSE; SODIUM BENZOATE; ISOMETHYL-.ALPHA.-IONONE; GERANIOL; BUTYLENE GLYCOL; JASMINUM OFFICINALE FLOWER; ALCOHOL; BUTYLATED HYDROXYTOLUENE; TOCOPHEROL; AFRAMOMUM ANGUSTIFOLIUM SEED; FERRIC OXIDE RED; FERRIC OXIDE YELLOW; FERROSOFERRIC OXIDE; WATER; CYCLOMETHICONE 5; CYCLOMETHICONE 6; DIMETHICONE; BUTYLENE GLYCOL DICAPRYLATE/DICAPRATE; PROPANEDIOL; LAURYL PEG-9 POLYDIMETHYLSILOXYETHYL DIMETHICONE; HEXAMETHYLENE DIISOCYANATE/TRIMETHYLOL HEXYLLACTONE CROSSPOLYMER; TRISILOXANE

CAPTURE DREAMSKIN FRESH & PERFECT CUSHION WITH SUNSCREEN BROAD SPECTRUM SPF 50 020

Active ingredients

Octinoxate 7.00%

Titanium dioxide 4.15%

Zinc oxide 9.80%

Purpose

Sunscreen

Uses

- Helps prevent sunburn.
- If used as directed with other sun protection measures (), decreases the risk of skin cancer and early skin aging caused by the sun. see Directions

Warnings

For external use only.

Do not use

on damaged or broken skin.

When using this product

keep out of eyes. Rinse with water to remove.

Stop use and ask a doctor if

rash occurs.

Keep out of reach of children.

If swallowed, get medical help or contact a Poison Control Center right away.

Directions

- Apply liberally 15 minutes before sun exposure.
- Reapply at least every 2 hours.
- Use a water-resistant sunscreen if swimming or sweating.
- Spending time in the sun increases your risk of skin cancer and early skin aging. To decreases this risk, regularly use a sunsreen with a broad spectrum SPF of 15 or higher and other sun protection measures including: Sun Protection Measures.
- limit time in the sun, especially from 10 a.m. - 2 p.m.
- wear long-sleeve shirts, pants, hats, and sunglasses.
- Children under 6 months of age: ask a doctor.

Other information

- Protect the product in this container from excessive heat and direct sun.

Inactive ingredients

AQUA (WATER), CYCLOPENTASILOXANE, CYCLOHEXASILOXANE, PEG-10 DIMETHICONE, DIMETHICONE, BUTYLENE GLYCOL DICAPRYLATE/DICAPRATE, PROPANEDIOL, LAURYL PEG-9 POLYDIMETHYLSILOXETHYL DIMETHICONE, HDI/TRIMETHYLOL HEXYLLACTONE CROSSPOLYMER, TRISILOXANE, PHENYL TRIMETHICONE, POLYMETHYL METHACRYLATE, GLYCERIN, SODIUM CHLORIDE, DIMETHICONE/PEG-/ CROSSPOLYMER, ALUMINUM HYDROXIDE, DISTEARDIMONIUM HECTORITE, PHENOXYETHANOL, STEARIC ACID, XYLITOL, TRIETHOXYCAPRYLYLSILANE, PARFUM (FRAGRANCE), CAPRYLYL GLYCOL, ETHYLHEXYLGLYCERIN, DISODIUM EDTA, SILICA, ZINC GLUCONATE, ADENOSINE, BUTYLPHENYL METHYLPROPIONAL, LIMONENE, SYNTHETIC FLUORPHLOGOPITE, PALMARIA PALMATA EXTRACT, SODIUM BENZOATE, ALPHA-ISOMETHYL IONONE, GERANIOL, BUTYLENE GLYCOL, JASMINUM OFFICINALE (JASMINE) FLOWER EXTRACT, ALCOHOL, HYDROGEN DIMETHICONE, BHT, SAPONINS, TOCOPHEROL, AFRAMOMUM ANGUSTIFOLIUM SEED EXTRACT. [MAY CONTAIN: CI 77491, CI 77492, CI 77499 (IRON OXIDES), CI 77891 (TITANIUM DIOXIDE)].